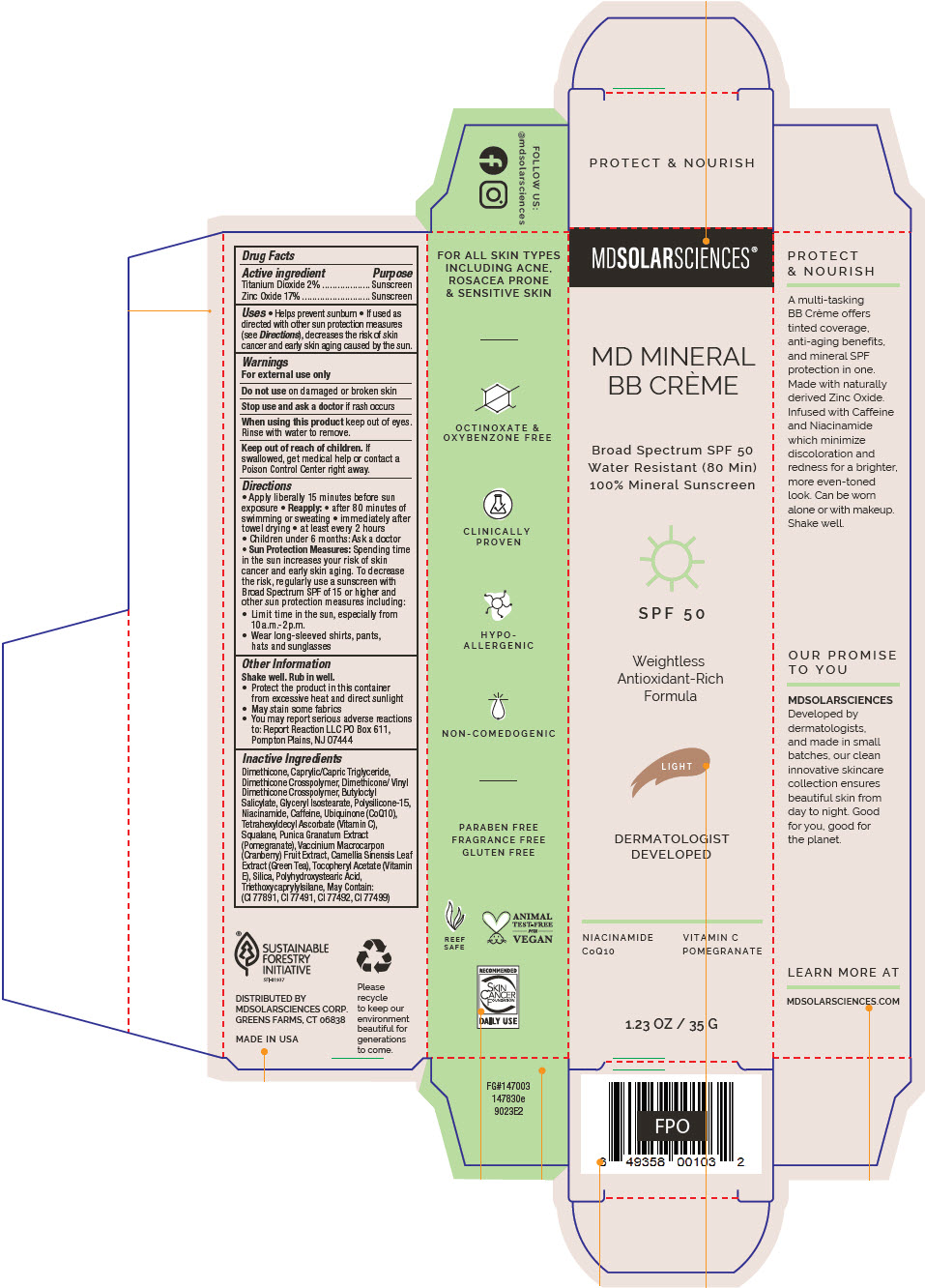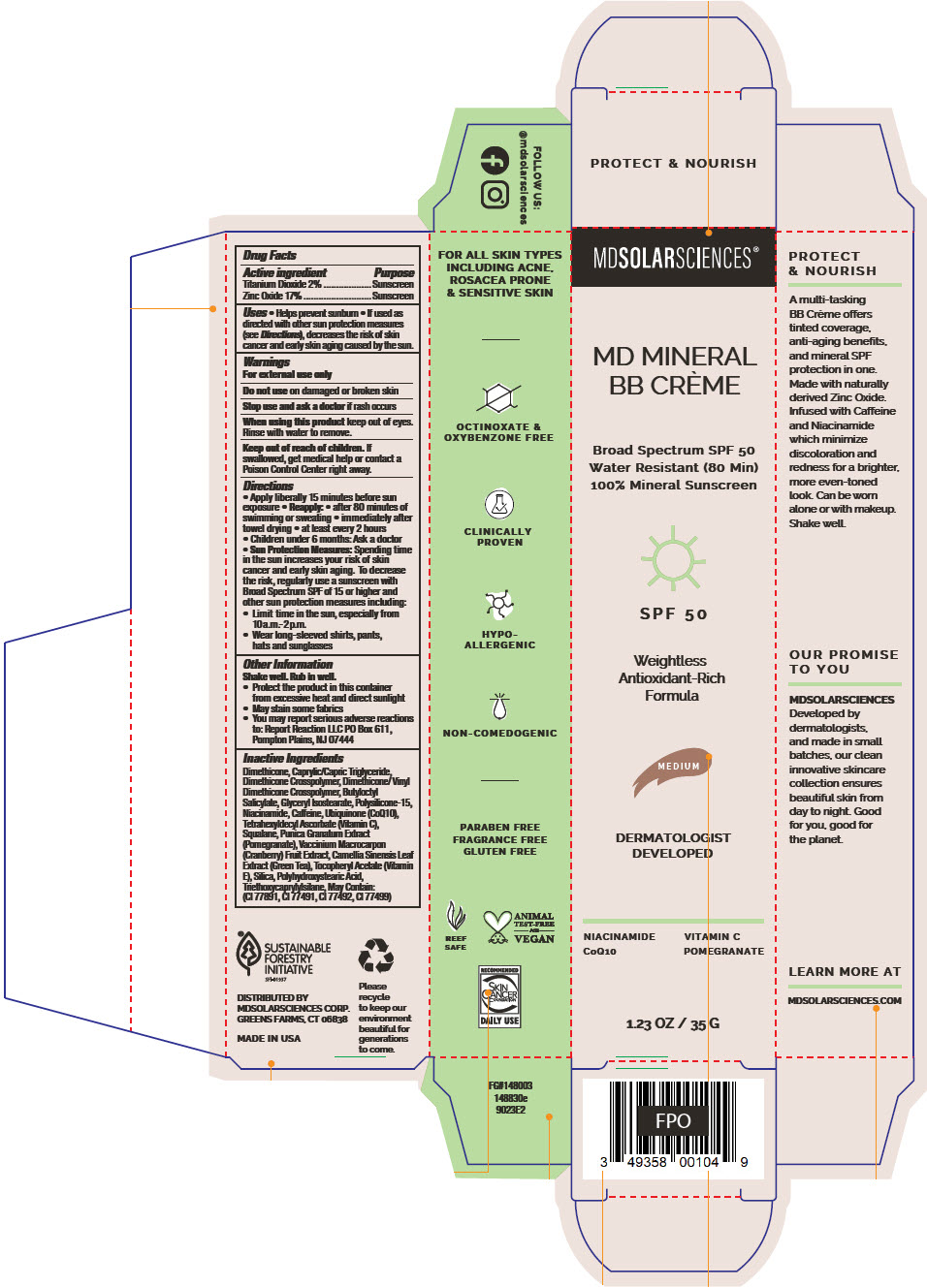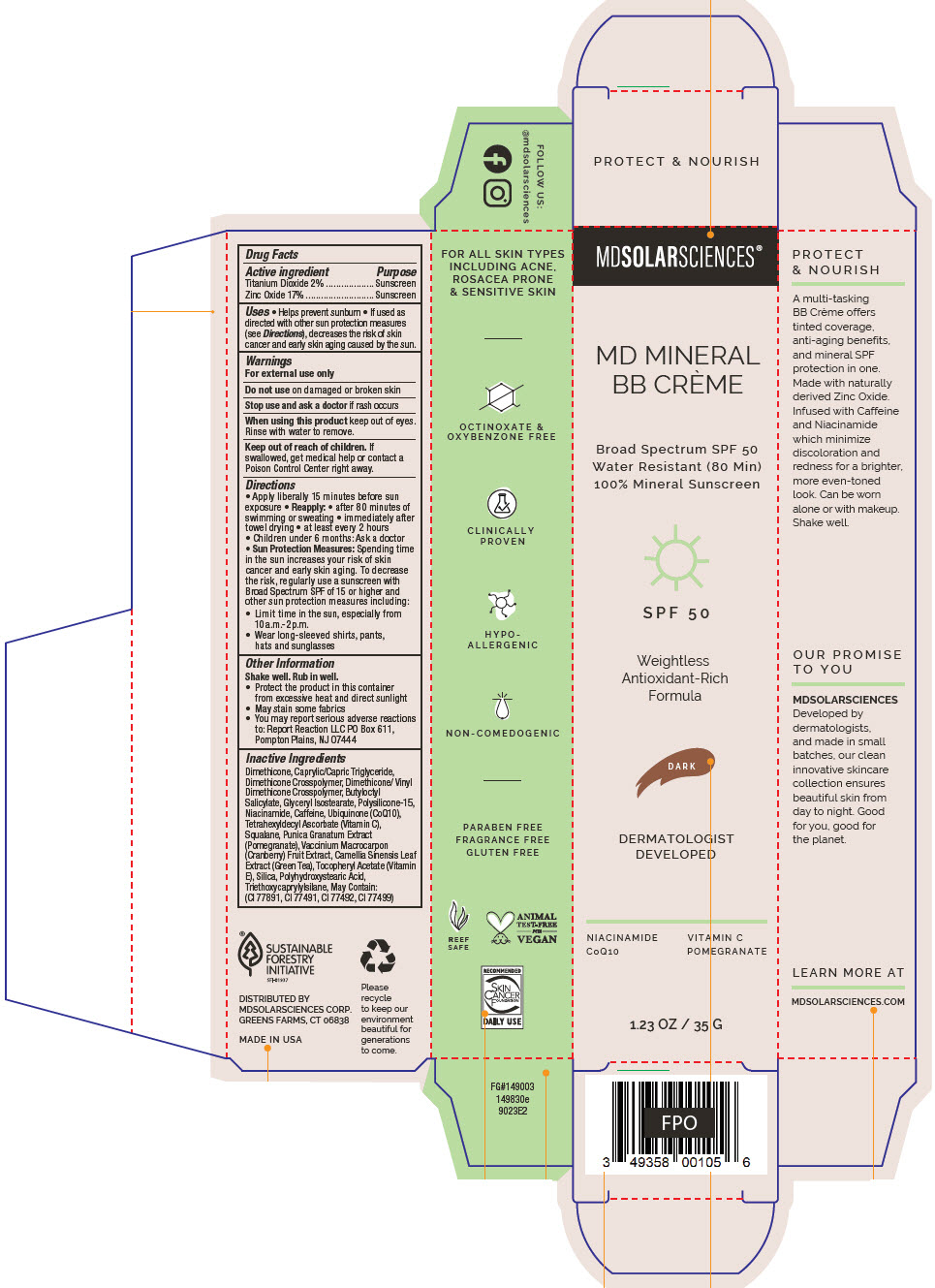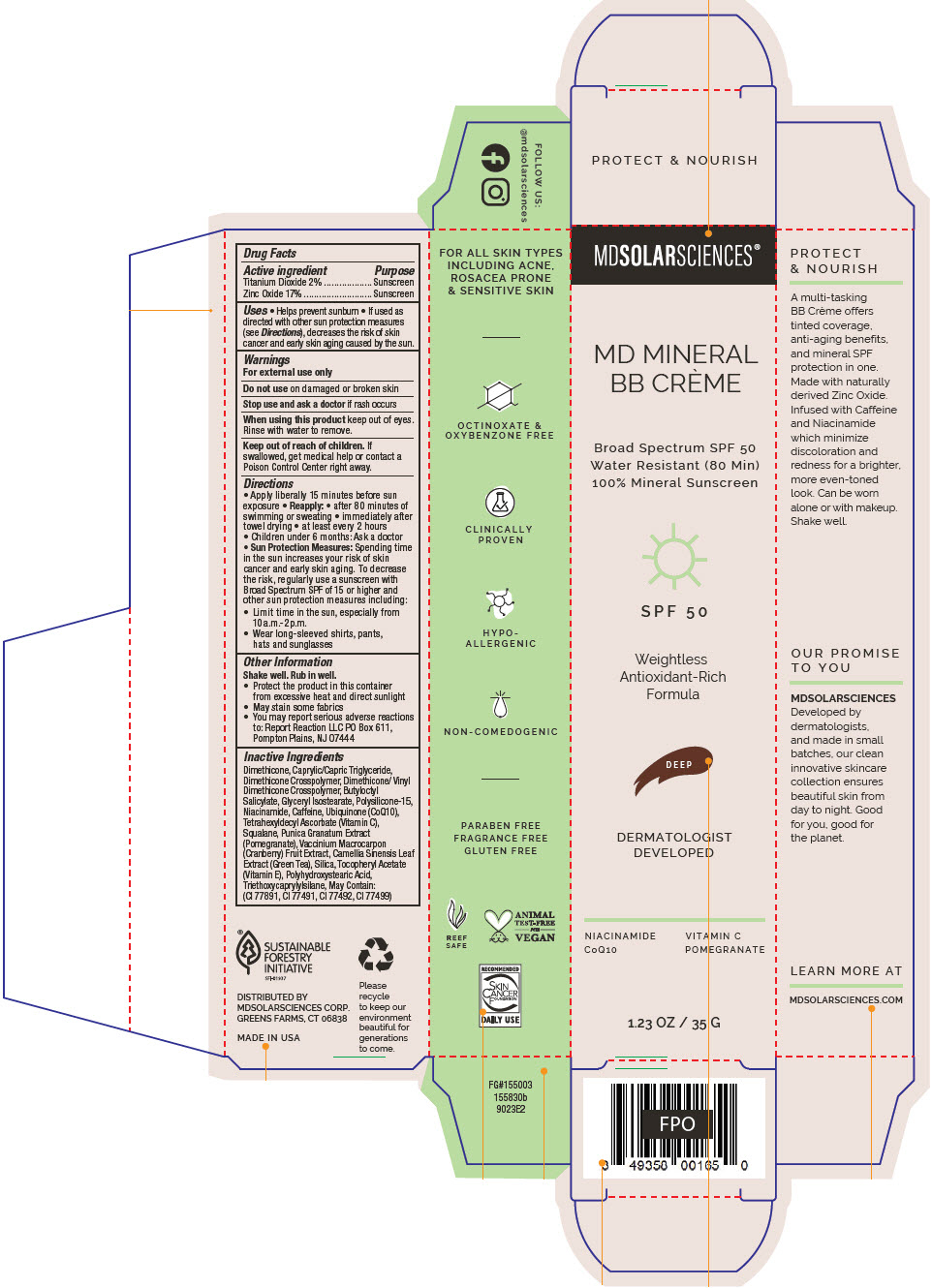 DRUG LABEL: MD Mineral BB Creme
NDC: 49358-572 | Form: CREAM
Manufacturer: MDSolarSciences
Category: otc | Type: HUMAN OTC DRUG LABEL
Date: 20251103

ACTIVE INGREDIENTS: TITANIUM DIOXIDE 2 g/100 g; ZINC OXIDE 17 g/100 g
INACTIVE INGREDIENTS: DIMETHICONE; MEDIUM-CHAIN TRIGLYCERIDES; DIMETHICONE/DIENE DIMETHICONE CROSSPOLYMER; DIMETHICONE/VINYL DIMETHICONE CROSSPOLYMER (SOFT PARTICLE); BUTYLOCTYL SALICYLATE; GLYCERYL ISOSTEARATE; POLYSILICONE-15; NIACINAMIDE; CAFFEINE; UBIDECARENONE; TETRAHEXYLDECYL ASCORBATE; SQUALANE; POMEGRANATE JUICE; CRANBERRY; GREEN TEA LEAF; .ALPHA.-TOCOPHEROL ACETATE; SILICON DIOXIDE; POLYHYDROXYSTEARIC ACID (2300 MW); TRIETHOXYCAPRYLYLSILANE

MD Mineral BB Crème
Broad Spectrum SPF 50 Water Resistant (80min) Mineral Sunscreen

Drug Facts

ACTIVE INGREDIENT

Active ingredient | Purpose
Titanium Dioxide 2% | Sunscreen
Zinc Oxide 17% | Sunscreen

Uses

- Helps prevent sunburn
- If used as directed with other sun protection measures (see Directions), decreases the risk of skin cancer and early skin aging caused by the sun.

Warnings

For external use only

Do not useon damaged or broken skin

Stop use and ask a doctorif rash occurs

WHEN USING

When using this productkeep out of eyes. Rinse with water to remove.

Keep out of reach of children.If swallowed, get medical help or contact a Poison Control Center right away.

Directions

- Apply liberally 15 minutes before sun exposure
- Reapply:
  - after 80 minutes of swimming or sweating
  - immediately after towel drying
  - at least every 2 hours
- Children under 6 months: Ask a doctor
- Sun Protection Measures:Spending time in the sun increases your risk of skin cancer and early skin aging. To decrease the risk, regularly use a sunscreen with Broad Spectrum SPF of 15 or higher and other sun protection measures including:
  - Limit time in the sun, especially from 10a.m.-2p.m.
  - Wear long-sleeved shirts, pants, hats and sunglasses

Other Information

Shake well. Rub in well.

- Protect the product in this container from excessive heat and direct sunlight
- May stain some fabrics
- You may report serious adverse reactions
  to: Report Reaction LLC PO Box 611,
  Pompton Plains, NJ 07444

Inactive Ingredients

Dimethicone, Caprylic/Capric Triglyceride, Dimethicone Crosspolymer, Dimethicone/ Vinyl Dimethicone Crosspolymer, Butyloctyl Salicylate, Glyceryl Isostearate, Polysilicone-15, Niacinamide, Caffeine, Ubiquinone (CoQ10), Tetrahexyldecyl Ascorbate (Vitamin C), Squalane, Punica Granatum Extract (Pomegranate), Vaccinium Macrocarpon (Cranberry) Fruit Extract, Camellia Sinensis Leaf Extract (Green Tea), Tocopheryl Acetate (Vitamin E), Silica, Polyhydroxystearic Acid, Triethoxycaprylylsilane, May Contain: (CI 77891, CI 77491, CI 77492, CI 77499)

DISTRIBUTED BY
MDSOLARSCIENCES CORP.
GREENS FARMS, CT 06838

PRINCIPAL DISPLAY PANEL - 35 G Tube Carton - LIGHT

MDSOLARSCIENCES®

MD MINERAL
BB CRÈME

Broad Spectrum SPF 50
Water Resistant (80 Min)
100% Mineral Sunscreen

SPF 50

Weightless
Antioxidant-Rich
Formula

LIGHT

DERMATOLOGIST
DEVELOPED

NIACINAMIDE
CoQ10

VITAMIN C
POMEGRANATE

1.23 OZ / 35 G

PRINCIPAL DISPLAY PANEL - 35 G Tube Carton - MEDIUM

MDSOLARSCIENCES®

MD MINERAL
BB CRÈME

Broad Spectrum SPF 50
Water Resistant (80 Min)
100% Mineral Sunscreen

SPF 50

Weightless
Antioxidant-Rich
Formula

MEDIUM

DERMATOLOGIST
DEVELOPED

NIACINAMIDE
CoQ10

VITAMIN C
POMEGRANATE

1.23 OZ / 35 G

PRINCIPAL DISPLAY PANEL - 35 G Tube Carton - DARK

MDSOLARSCIENCES®

MD MINERAL
BB CRÈME

Broad Spectrum SPF 50
Water Resistant (80 Min)
100% Mineral Sunscreen

SPF 50

Weightless
Antioxidant-Rich
Formula

DARK

DERMATOLOGIST
DEVELOPED

NIACINAMIDE
CoQ10

VITAMIN C
POMEGRANATE

1.23 OZ / 35 G

PRINCIPAL DISPLAY PANEL - 35 G Tube Carton - DEEP

MDSOLARSCIENCES®

MD MINERAL
BB CRÈME

Broad Spectrum SPF 50
Water Resistant (80 Min)
100% Mineral Sunscreen

SPF 50

Weightless
Antioxidant-Rich
Formula

DEEP

DERMATOLOGIST
DEVELOPED

NIACINAMIDE
CoQ10

VITAMIN C
POMEGRANATE

1.23 OZ / 35 G